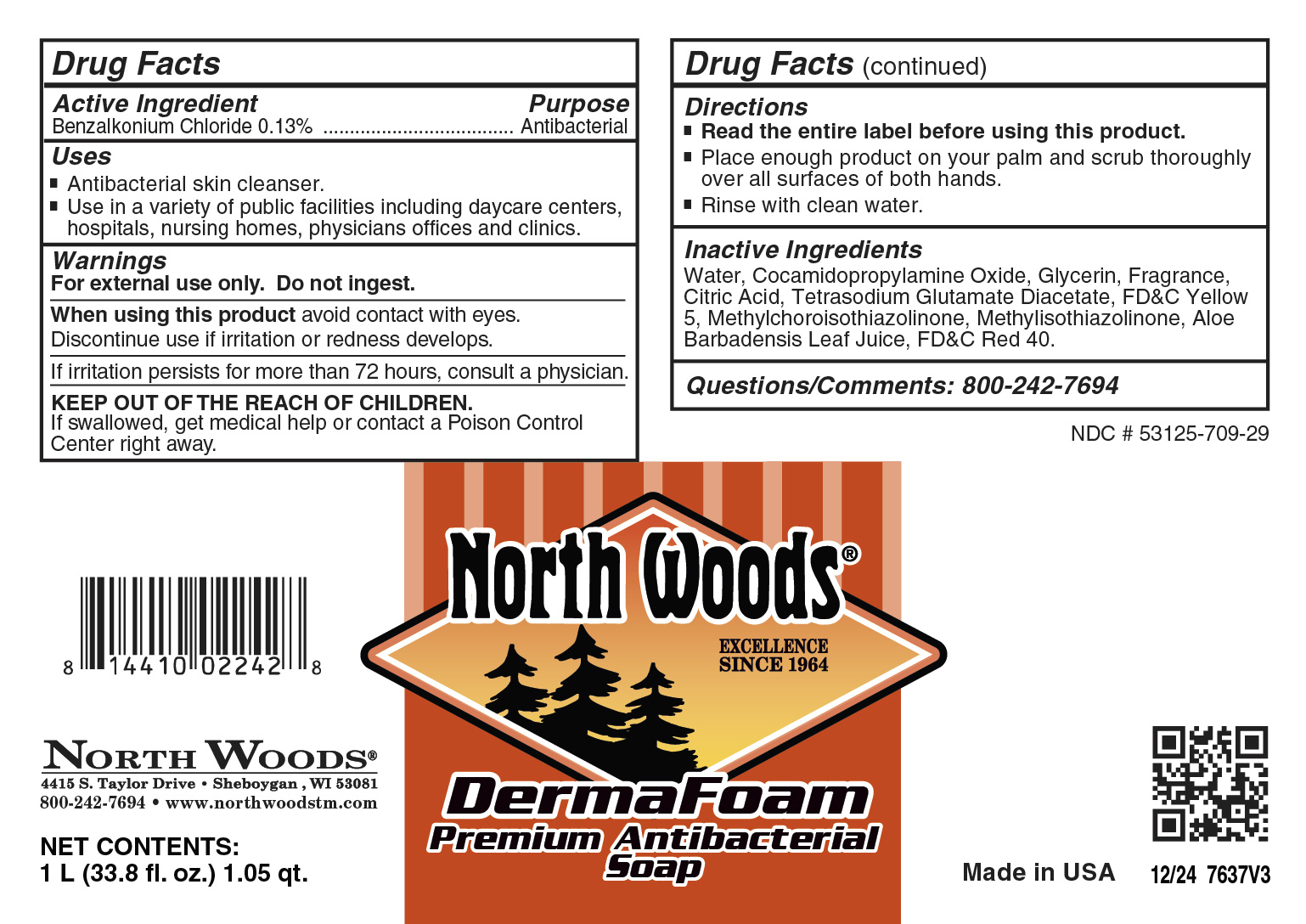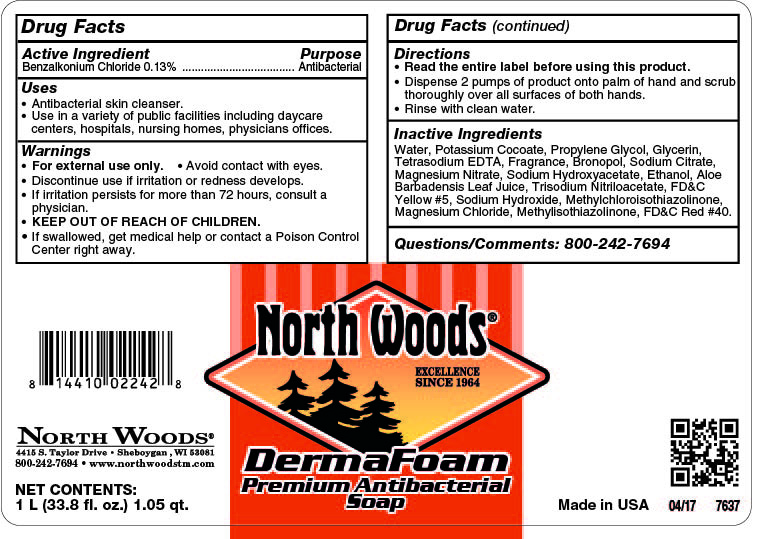 DRUG LABEL: DermaFoam Premium Antibacterial
NDC: 53125-709 | Form: SOAP
Manufacturer: Superior Chemical Corporation
Category: otc | Type: HUMAN OTC DRUG LABEL
Date: 20241120

ACTIVE INGREDIENTS: BENZALKONIUM CHLORIDE 0.13 mg/1 mL
INACTIVE INGREDIENTS: LIMONENE, (+)-; WATER; GLYCERIN; FD&C YELLOW NO. 5; METHYLCHLOROISOTHIAZOLINONE; METHYLISOTHIAZOLINONE; FD&C RED NO. 40; CITRAL; 2-TERT-BUTYLCYCLOHEXYL ACETATE; GERANIOL; ALOE BARBADENSIS LEAF JUICE; MAGNESIUM NITRATE; ALLYL HEPTANOATE; TETRASODIUM GLUTAMATE DIACETATE; 2-TERT-BUTYLCYCLOHEXYLOXYBUTANOL; 4-CYCLOHEXYL-2-METHYL-2-BUTANOL; LINALOOL; HYDROGEN PEROXIDE; COCAMIDOPROPYLAMINE OXIDE; ANHYDROUS CITRIC ACID; 2,6-DIMETHYLOCTAN-2-OL

North Woods DermaFoam Premium Antibacterial

Active Ingredient

Triclosan 0.30%

Uses

- Antibacterial hand cleaner.
- Use in a variet of public facilities including daycare centers, hospitals, nursing homes, physicians offices.

Warnings

- For external use only.
- Avoid contact with eyes.
- Children under the age of 6 should be supervised by an adult when using this product.
- Discontinue use is irritation or redness develops.
- If irritation persists for more than 72 hours, consult a physician.
- KEEP OUT OF REACH OF CHILDREN.

Directions

- Read the entire label before using this product.
- Dispense 0.8 mL of product onto wet palm.
- Rub hands together to distribute product, then rinse hands with clean.

Inactive Ingredients

Water, Potasium cocoate (contains coconut), Propylene Glycol, Glycerine, DMDM Hydantoin, Fragrance, FD&C Yellow #5, Aloe Barbadensis Leaf Juice. FD&C Red #40.

Questions or Comments? Phone: (800) 777-9343

MDS information:(800) 891-4965

Purpose

Antibacterial

KEEP OUT OF REACH OF CHILDREN

PACKAGE LABEL

75129-00_Derma Foam Premium Antibacterial